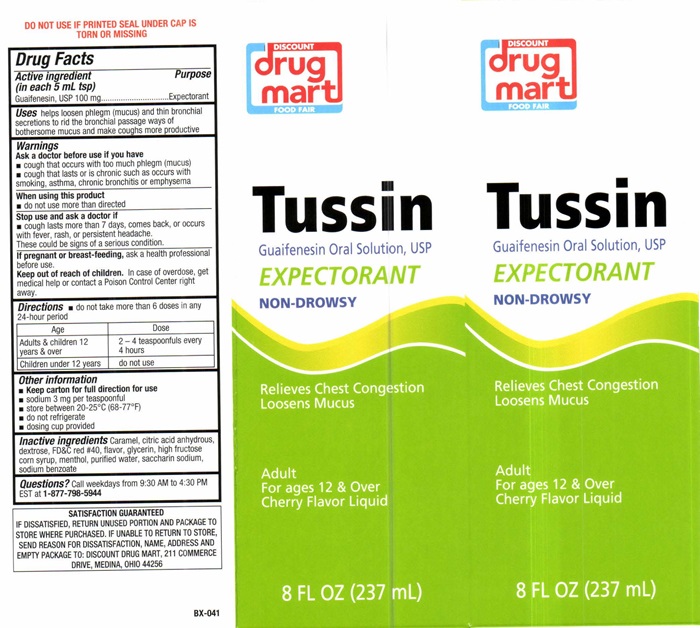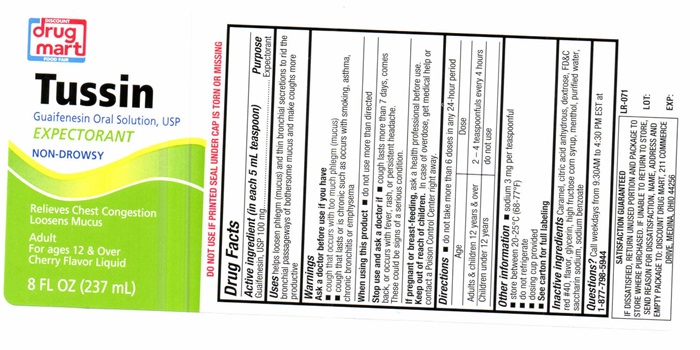 DRUG LABEL: Tussin
NDC: 53943-507 | Form: LIQUID
Manufacturer: Discount Drug Mart
Category: otc | Type: HUMAN OTC DRUG LABEL
Date: 20251223

ACTIVE INGREDIENTS: GUAIFENESIN 100 mg/5 mL
INACTIVE INGREDIENTS: CARAMEL; ANHYDROUS CITRIC ACID; DEXTROSE; FD&C RED NO. 40; GLYCERIN; HIGH FRUCTOSE CORN SYRUP; MENTHOL; WATER; SACCHARIN SODIUM; SODIUM BENZOATE

Drug Facts Active ingredient (in each 5 mL tsp)

Guaifenesin, USP 100 mg

Purpose

Expectorant

Keep out of reach of children. In case of overdose, get medical help or contact a Poison Control Center right away.

Uses

helps loosen phlegm (mucus) and thin bronchial secretions to rid the passage ways of bothersome mucus and make cough more productive

Warnings

DO NOT USE IF PRINTED SEAL UNDER CAP IS TORN OR MISSING

Ask a doctor if you have

- cough that occurs with too much phlegm (mucus)
- cough that lasts or is chronic such as occurs with smoking, asthma, chronic bronchitis or emphysema

When using this product

- do not use more than directed

Stop use and ask a doctor if

- cough lasts more than 7 days, comes back, or occurs with fever, rash, or persistant headache.

These could be signs of a serious condition.

if pregnant or breast-feeding,

ask a health professional before use.

Directions

- do not take more than 6 doses in any 24-hour period

Age | Dose
Adults and children 12 years and over | 2 - 4 teaspoonfuls every 4 hours
Children under 12 years | do not use

Other information

- Keep carton for full Directions for use.

- sodium 3 mg per teaspoonful
- store at 20°-25°C (68°-77°F)
- do not refrigerate
- dosing cup provided

Inactive ingredients

Carmel, citric acid anhydrous, dextrose, FD and red # 40, flavor, glycerin, high fructose corn syrup, menthol, purified water, saccharin sodium, sodium benzoate

Questions?

Call weekdays from 9:30 AM to 4:30 PM EST at 1-877-798-5944

DISCOUNT drug mart FOOD FAIR Tussin product label

DISCOUNT

drug mart

FOOD FAIR

Tussin

Guaifenesin Oral Solution, USP

EXPECTORANT

NON-DROWSY

Relieves Chest Congestion

Loosens Mucus

Adutl

For ages 12 and Over

Cherry Flavored Liquid

8 FL OZ (237 mL)

BX-041 LOT: EXP:

SATISFACTION GUARANTEED
IF DISSASIFIED , RETURN UNUSED PORTION AND PACKAGE TO STORE WHERE PURCHASED. IF UNABLE TO RETURN TO STORE, SEND REASON FOR DISSATISFACTION, NAME, ADDRESS AND EMPTY PACKAGE TO: DISCOUNT DRUG MART, 211 COMMERCE DRIVE, MEDINA, OHIO 44256

res